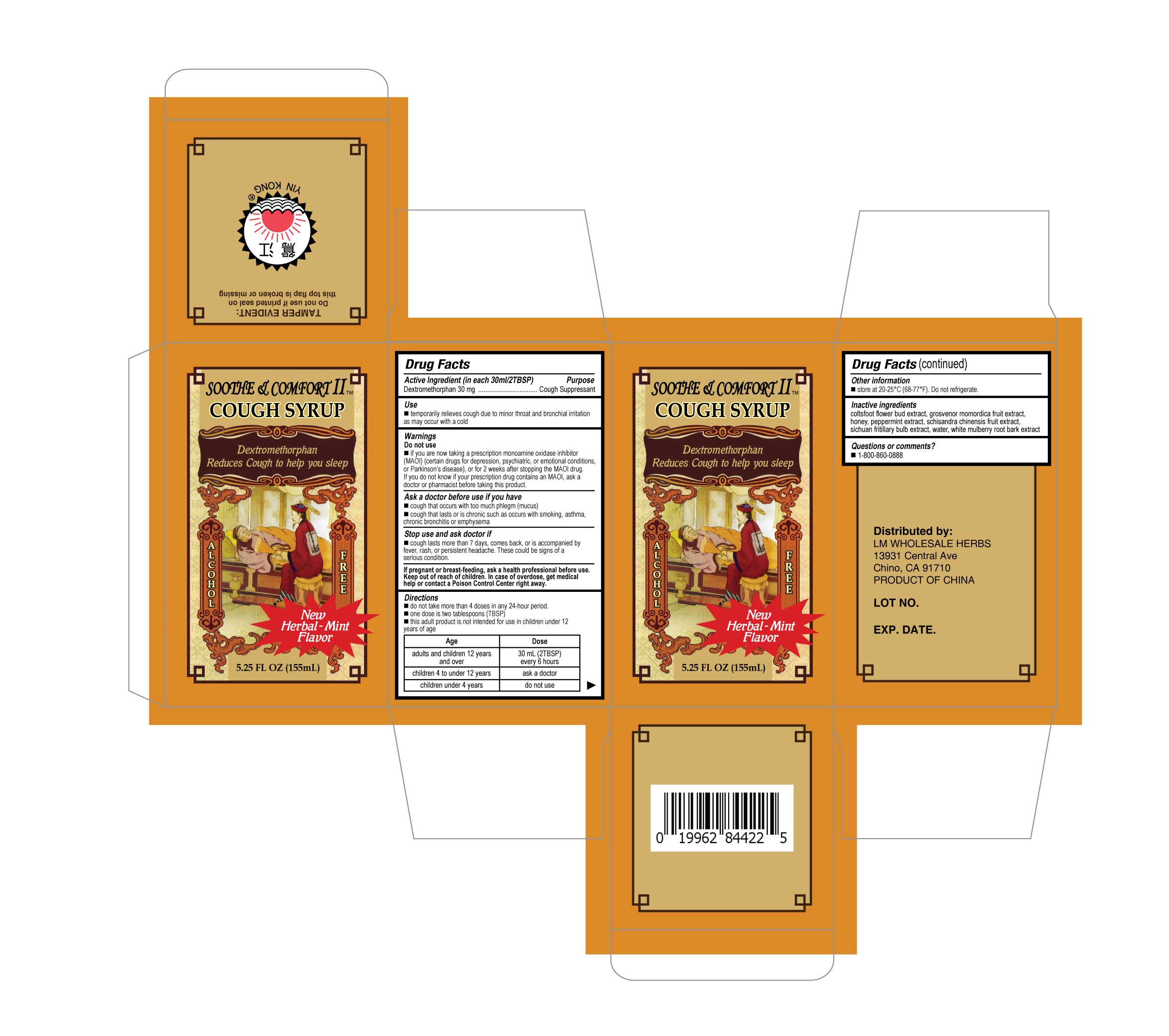 DRUG LABEL: Soothe Comfort II Cough Syrup
NDC: 75663-005 | Form: LIQUID
Manufacturer: LM WHOLESALE HERBS
Category: otc | Type: HUMAN OTC DRUG LABEL
Date: 20210428

ACTIVE INGREDIENTS: DEXTROMETHORPHAN 30 mg/30 mL
INACTIVE INGREDIENTS: MORUS ALBA ROOT BARK; TUSSILAGO FARFARA FLOWER BUD; HONEY; FRITILLARIA PRZEWALSKII BULB; SCHISANDRA CHINENSIS FRUIT OIL; SIRAITIA GROSVENORII FRUIT; WATER; PEPPERMINT OIL

LMSootheComfortIICghSyrp

Active ingredient (in each 30 ml/2TBSP)

Dextromethorphan 30 mg

Purpose

Cough suppressant

Use

■ temporarily relieves cough due to minor throat and bronchial irritation as may occur with a cold

Warnings

Do not use

■ if you are now taking a prescription monoamine oxidase inhibitor (MAOI) (certain drugs for depression, psychiatric, or emotional conditions, or Parkinson's disease), or for 2 weeks after stopping the MAOI drug. If you do not know if your prescription drug contains an MAOI, ask a doctor or pharmacist before taking this product.

Ask a doctor before use if you have

■cough that occurs with too much phlegm (mucus)

■cough that lasts or is chronic such as occurs with smoking, asthma, chronic bronchitis or emphysema

Stop use and ask a doctor if

■ cough lasts more than 7 days, comes back, or is accompanied by fever, rash, or persistent headache. These could be signs of a serious condition.

If pregnant or breast-feeding

ask a health professional before use

Keep out of reach of children

In case of overdose, get medical help or contact a Poison Control Center right away.

Directions

■ do not take more than 4 doses in any 24-hour period

■ one dose is two tablespoons (TBSP)

■ this adult product is not intended for use in children under 12 years of age

Age Dose

adults and children 12 years 30 mL (2TBSP)

and over every 6 hours

children 4 to under 12 years ask a doctor

children under 4 years do not use

Other Information

■ store at 20-25ºC (68-77ºF). Do not refrigerate

Inactive ingredients

coltsfoot flower bud extract, grosvenor momordica fruit extract, honey, peppermint extract, schisandra chinensis fruit extract, sichuan fritillary bulb extract, water, white mulberry root bark extract

Questions or comments?

■ 1-800-860-0888